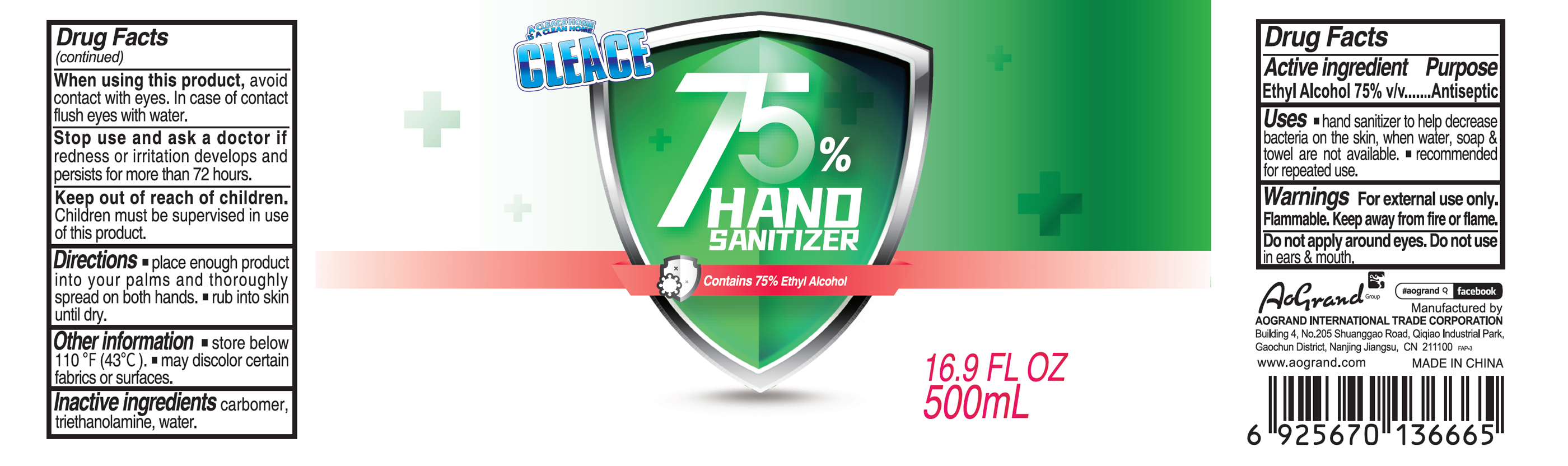 DRUG LABEL: CLEACE 75% Alcohol hand sanitizer
NDC: 80125-002 | Form: GEL
Manufacturer: Warehouse Agency Llc
Category: otc | Type: HUMAN OTC DRUG LABEL
Date: 20230213

ACTIVE INGREDIENTS: ALCOHOL 75 mL/100 mL
INACTIVE INGREDIENTS: CARBOMER HOMOPOLYMER, UNSPECIFIED TYPE; WATER; TROLAMINE

CLEACE 75% Alcohol hand sanitizer

Active Ingredient

Alcohol 75% v/v. Purpose: Antiseptic

Purpose

Antiseptic, Hand Sanitizer

Uses

- hand sanitizer to help decrease bacteria on the skin, when water, soap & towel are not available.
- recommended for repeated use.

Warnings

For external use only.

Flammable. Keep away from fire or flame.

Do not apply around eyes.

Do not use in ears & mouth.

When using this product

avoid contact with eyes. In case of contact flush eyes with water.

Stop use and ask a doctor if

redness or irritation develop and persist for more than 72 hours

Keep out of reach of children.

Children must be supervised in use of this product.

Directions

- place enough product into your palms and thoroughly spread on both hands.
- rub into skin until dry.

Other information

- store below 110F (43C)
- may discolor certain fabrics or surfaces.

Inactive ingredients

Carbomer, Triethanolamine, Water

Package Label - Principal Display Panel

500 mL NDC: 80125-002-01

A CLEACE HOME

IS A CLEAN HOME

CLEACE

75% HAND SANITIZER

Contains 75% Ethyl Alcohol

16.9 FL OZ

500mL